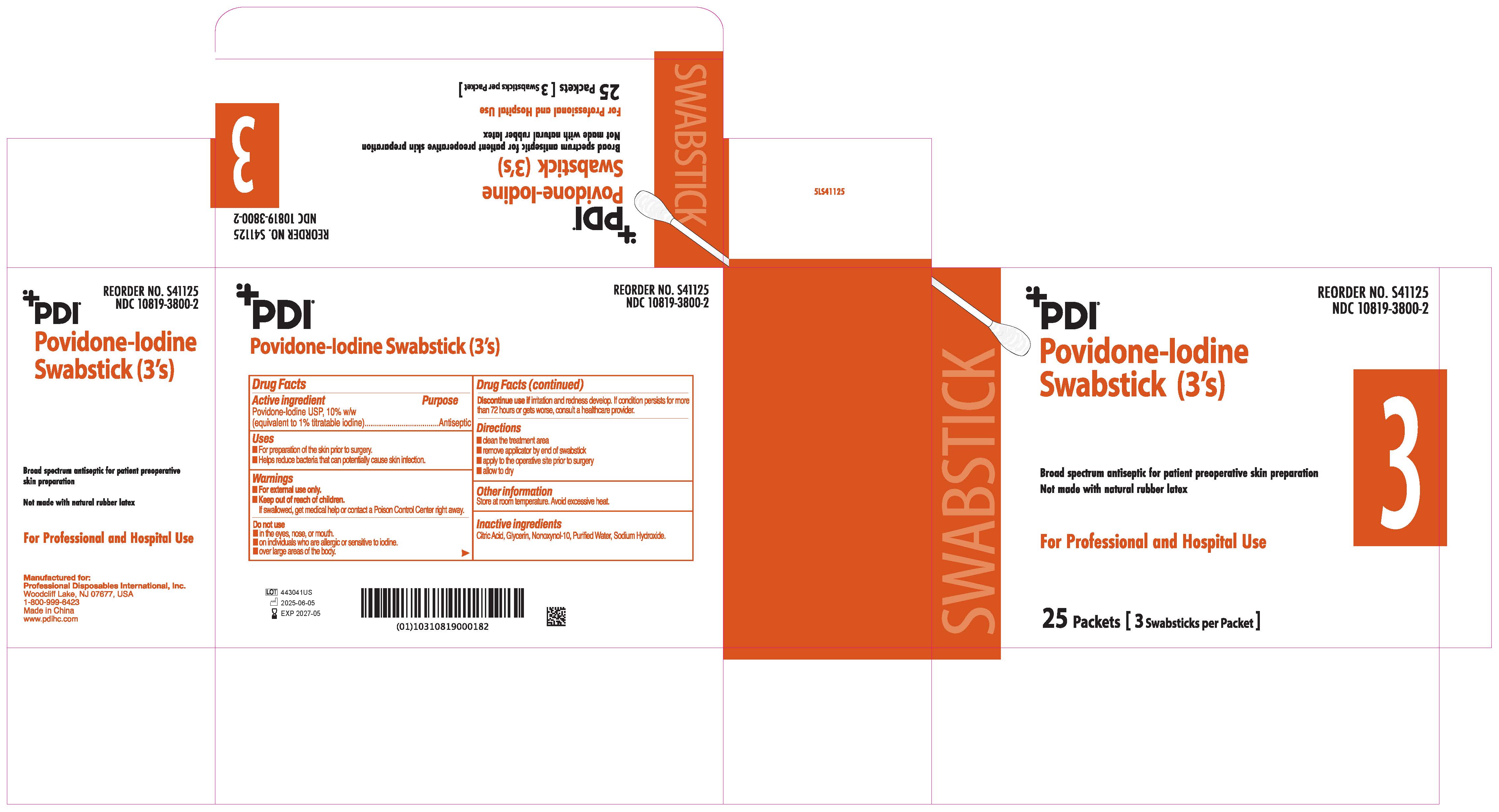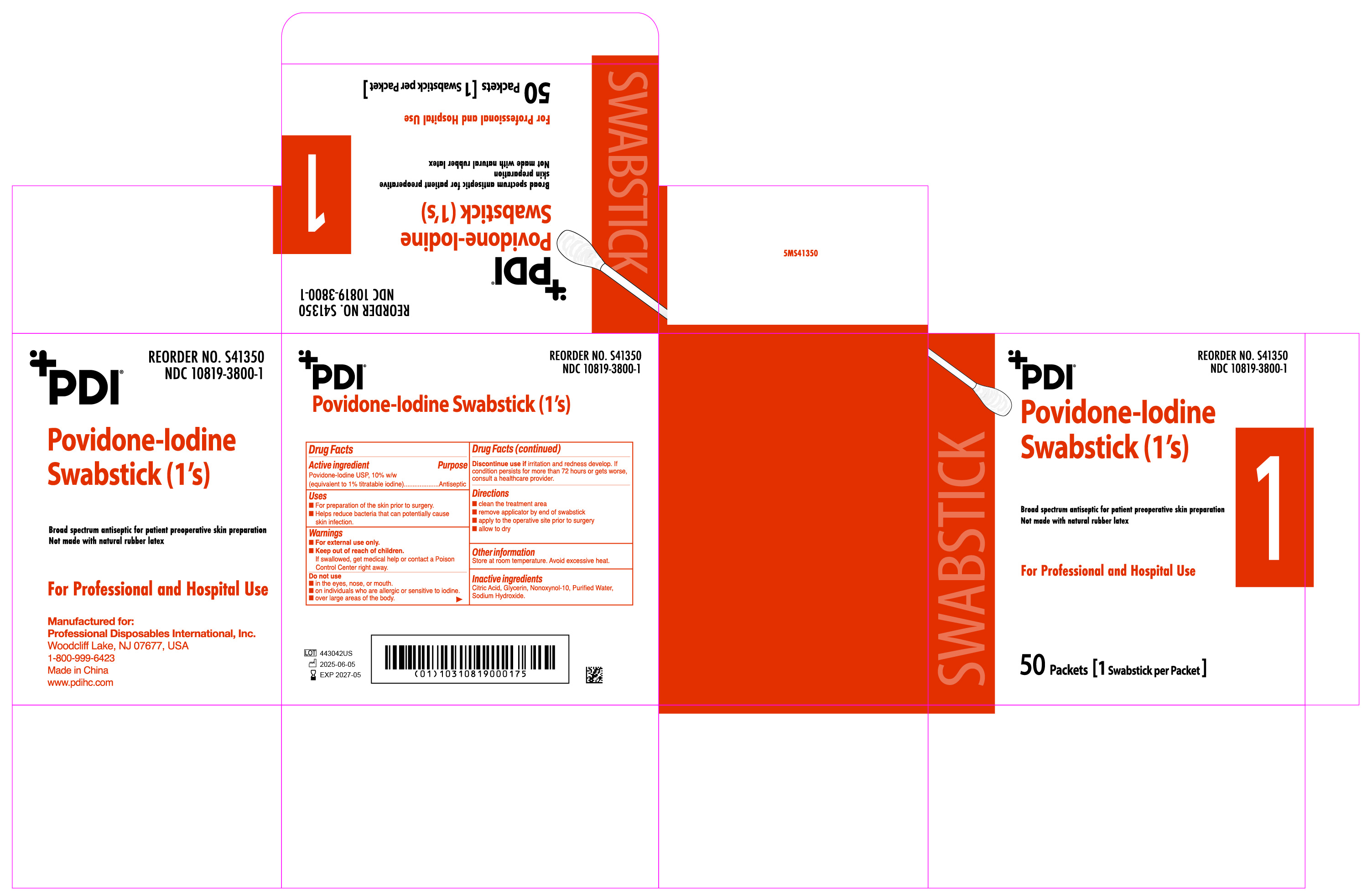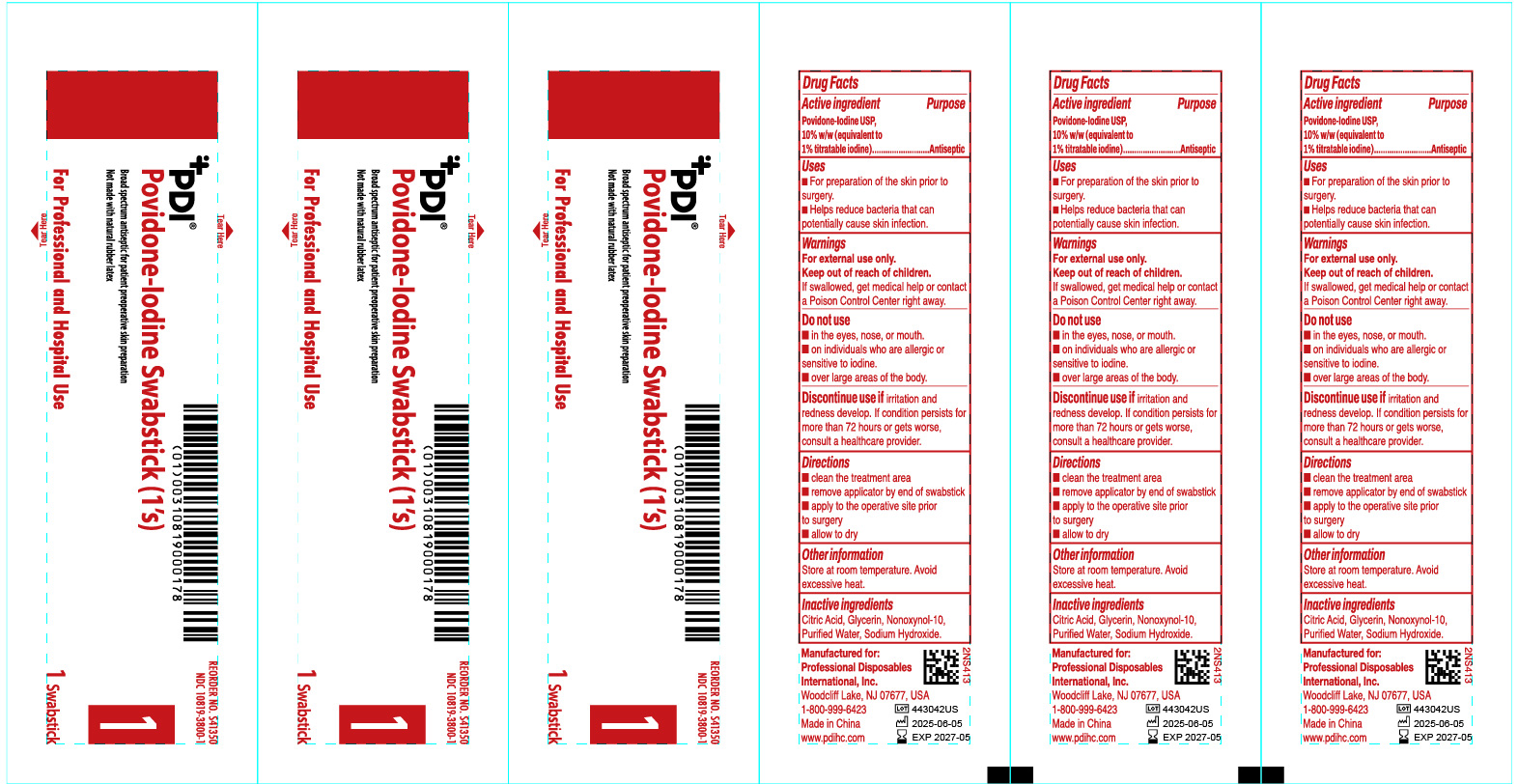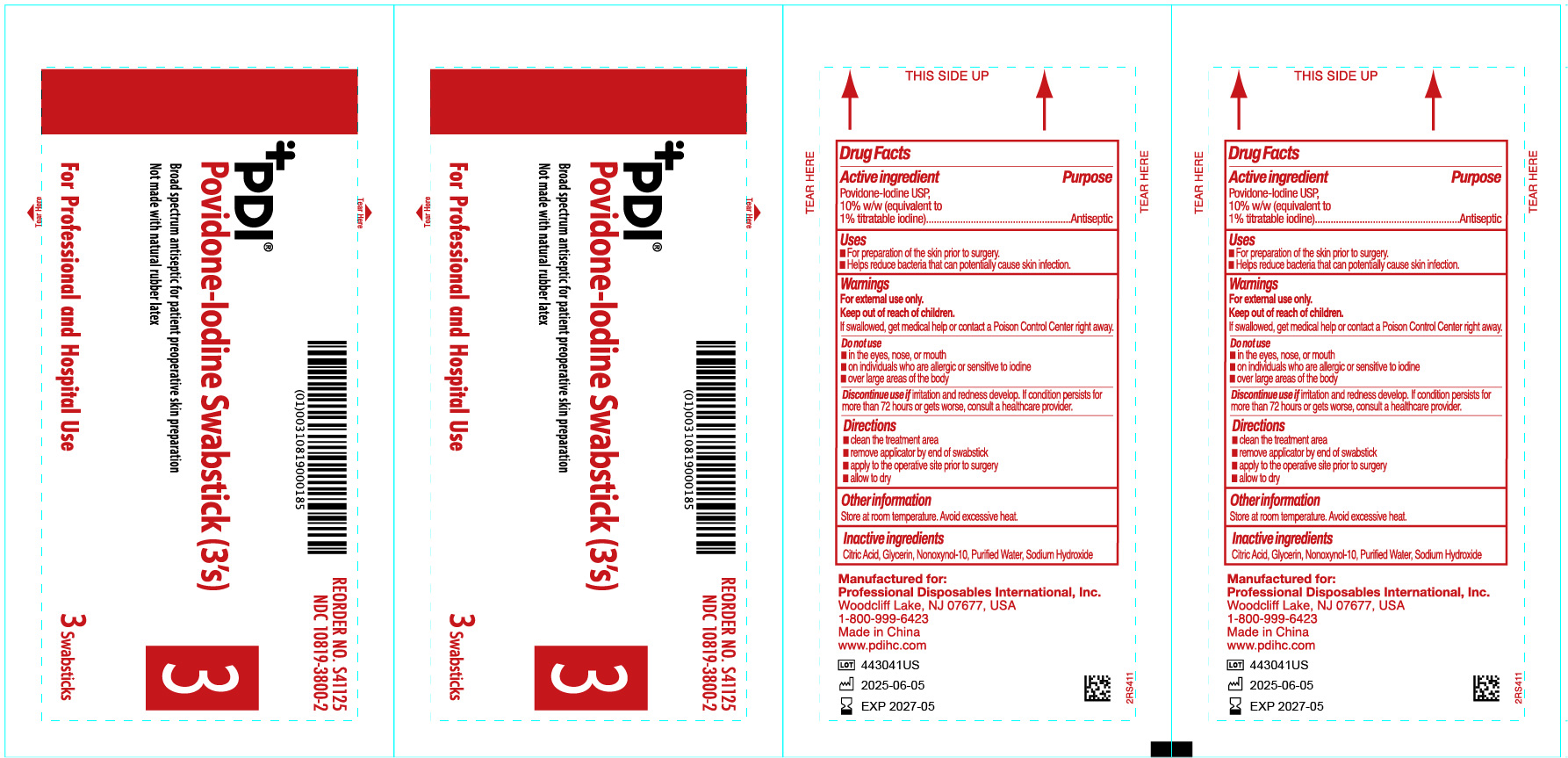 DRUG LABEL: Povidone-Iodine Swabstick
NDC: 10819-3800 | Form: STICK
Manufacturer: Professional Disposables International, Inc.
Category: otc | Type: HUMAN OTC DRUG LABEL
Date: 20260217

ACTIVE INGREDIENTS: POVIDONE-IODINE 10 mg/1 mL
INACTIVE INGREDIENTS: WATER; SODIUM HYDROXIDE; CITRIC ACID MONOHYDRATE; NONOXYNOL-10; GLYCERIN

JEK PVP-I Swabstick (1's) and (3's)

Active ingredient

Povidone-Iodine USP 10% w/w (equivalent to 1.0% titratable iodine)

Purpose

Antiseptic

Uses

- For preparation of the skin prior to surgery
- Helps reduce bacteria that can potentially cause skin infection

Warnings

For external use only

If swallowed, get medical help or contact a Poison Control Center right away.

Discontinue use if irritation and redness develop. If condition persists for more than 72 hours or gets worse, consult a healthcare provider.

Directions

For preparation of the skin prior to surgery

- clean the treatment area
- remove applicator by end of swabstick
- apply to the operative site prior to surgery
- allow to dry

Other information

- Store at room temperature
- Avoid excessive heat

Inactive ingredients

Citric Acid, Glycerin, Nonoxynol-10, Purified Water, Sodium Hydroxide

Do not use

- in the eyes, nose or mouth
- on individuals who are allergic or sensitive to iodine
- over large areas of the body

Keep out of reach of children

PACKAGE LABEL

S41350 web NDC# 10819-3800-1

S41350 box NDC# 10819-3800-1

S41125 web NDC# 10819-3800-2

S41125 box NDC# 10819-3800-2